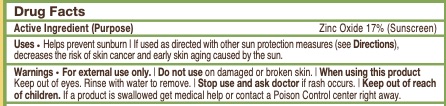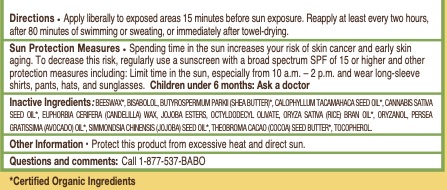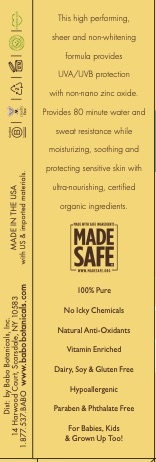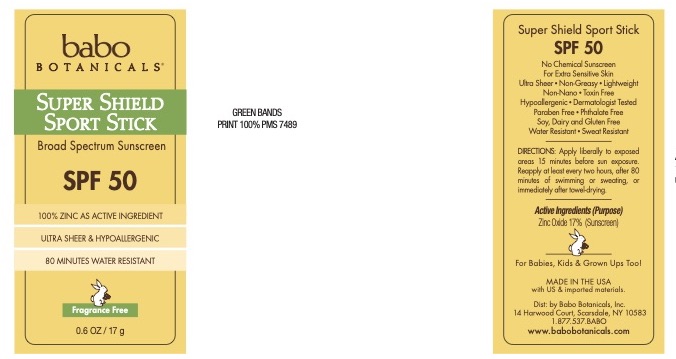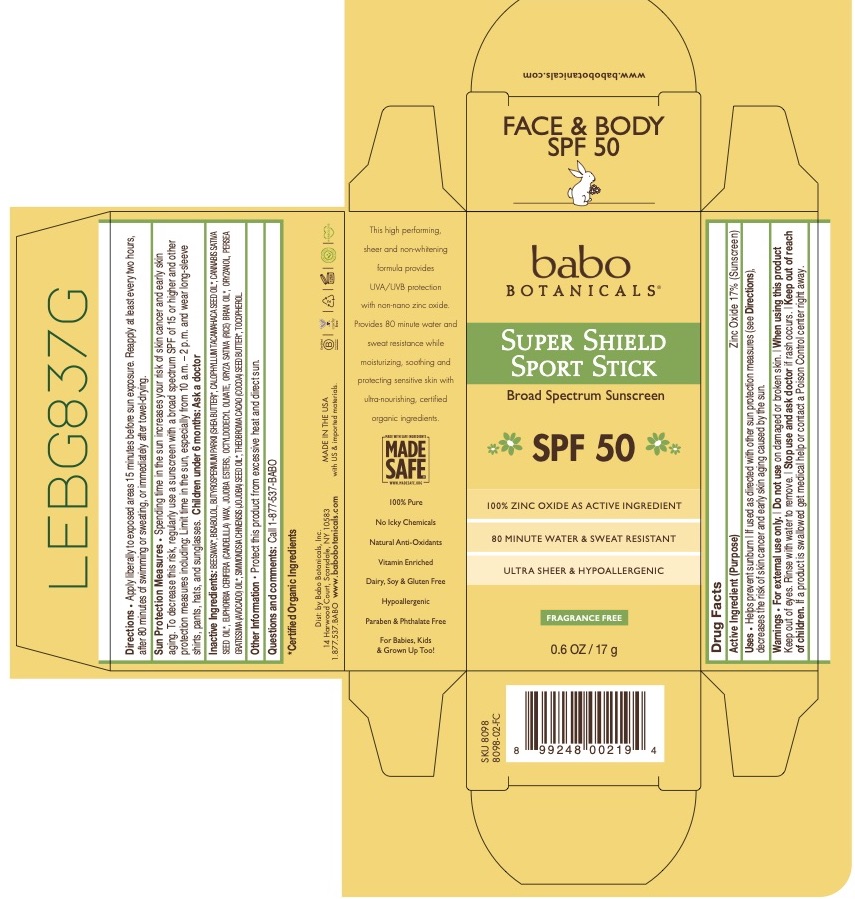 DRUG LABEL: SPF 50 Super Shield Sport Sunscreen
NDC: 79265-8098 | Form: STICK
Manufacturer: Babo Botanicals, Inc.
Category: otc | Type: HUMAN OTC DRUG LABEL
Date: 20241212

ACTIVE INGREDIENTS: ZINC OXIDE 17.363 g/100 g
INACTIVE INGREDIENTS: SHEA BUTTER 1 mL/100 g; CANNABIS SATIVA SEED OIL 0.01 mL/100 g; HYDROGENATED JOJOBA OIL, RANDOMIZED 0.537 mL/100 g; RICE BRAN OIL 27.38 mL/100 g; AVOCADO OIL 15 mL/100 g; JOJOBA OIL 7.5 mL/100 g; ORYZANOL 3 mL/100 g; WHITE WAX 6 mL/100 g; CANDELILLA WAX 9.5 mL/100 g; OCTYLDODECYL OLEATE 8.75 mL/100 g; TOCOPHEROL 0.75 mL/100 g; LEVOMENOL 0.2 mL/100 g; CALOPHYLLUM TACAMAHACA SEED OIL 0.01 mL/100 g; COCOA BUTTER 3 mL/100 g

8098 Babo Botanicals SPF 50 Super Shield Sport Stick Sunscreen

Primary Container Labeling

79265-8098-1 17 g

79265-8098 SPF 50 Super Shield Sport Stick Sunscreen

Sunscreen product manufactured pursuant to the Final Monograph. Active ingredient Zinc Oxide.

Active Ingredient

Zinc Oxide 17.363%

Uses

Helps prevent sunburn. • If used as directed with other sun protection measures (see Directions), decreases the risk of skin cancer and early skin aging caused by the sun.

Purpose

Sunscreen

Warnings

For external use only • Do not use on damaged or broken skin. • When using this product Keep out of eyes. Rinse with water to remove. • Stop use and ask doctor if rash occurs. • Keep out of reach of children. If a product is swallowed get medical help or contact a Poison Control center right away.

Do not use

on damaged or broken skin.

When using this product Keep out of eyes. Rinse with water to remove.

Stop use and ask doctor if rash occurs. •

Keep out of reach of children. If a product is swallowed get medical help or contact a Poison Control center right away.

Directions

Apply liberally to exposed areas 15 minutes before sun exposure. Reapply at least every two hours, after 80 minutes of swimming or sweating, or immediately after towel-drying.

inactive Ingredients

BEESWAX*
BISABOLOL
BUTYROSPERMUM PARKII (SHEA) BUTTER*
CALOPHYLLUM TACAMAHACA SEED OIL*
CANNABIS SATIVA SEED OIL*
EUPHORBIA CERIFERA (CANDELILLA) WAX
JOJOBA ESTERS
OCTYLDODECYL OLEATE
ORYZA SATIVA (RICE) BRAN OIL*
ORYZANOL
PERSEA GRATISSIMA (AVOCADO) OIL*
SIMMONDSIA CHINENSIS (JOJOBA) SEED OIL*
THEOBROMA CACAO (COCOA) SEED BUTTER*
TOCOPHEROL

*Certified Organic ingredient

Other Information

Other Information: Protect this product from excessive heat and direct sun

QUESTIONS/ COMMENTS?

Questions and comments?

Call 1-877-537-BABO

PRINCIPAL DISPLAY PANEL

79265-8098-0

Babo Botanicals

Super Shield Sport Stick

Broad Spectrum Sunscreen SPF 50

100% Zinc Oxide Active Ingredient

80 Minute Water & Sweat Resistant

Ultra Sheer & Hypoallergenic

Fragrance Free